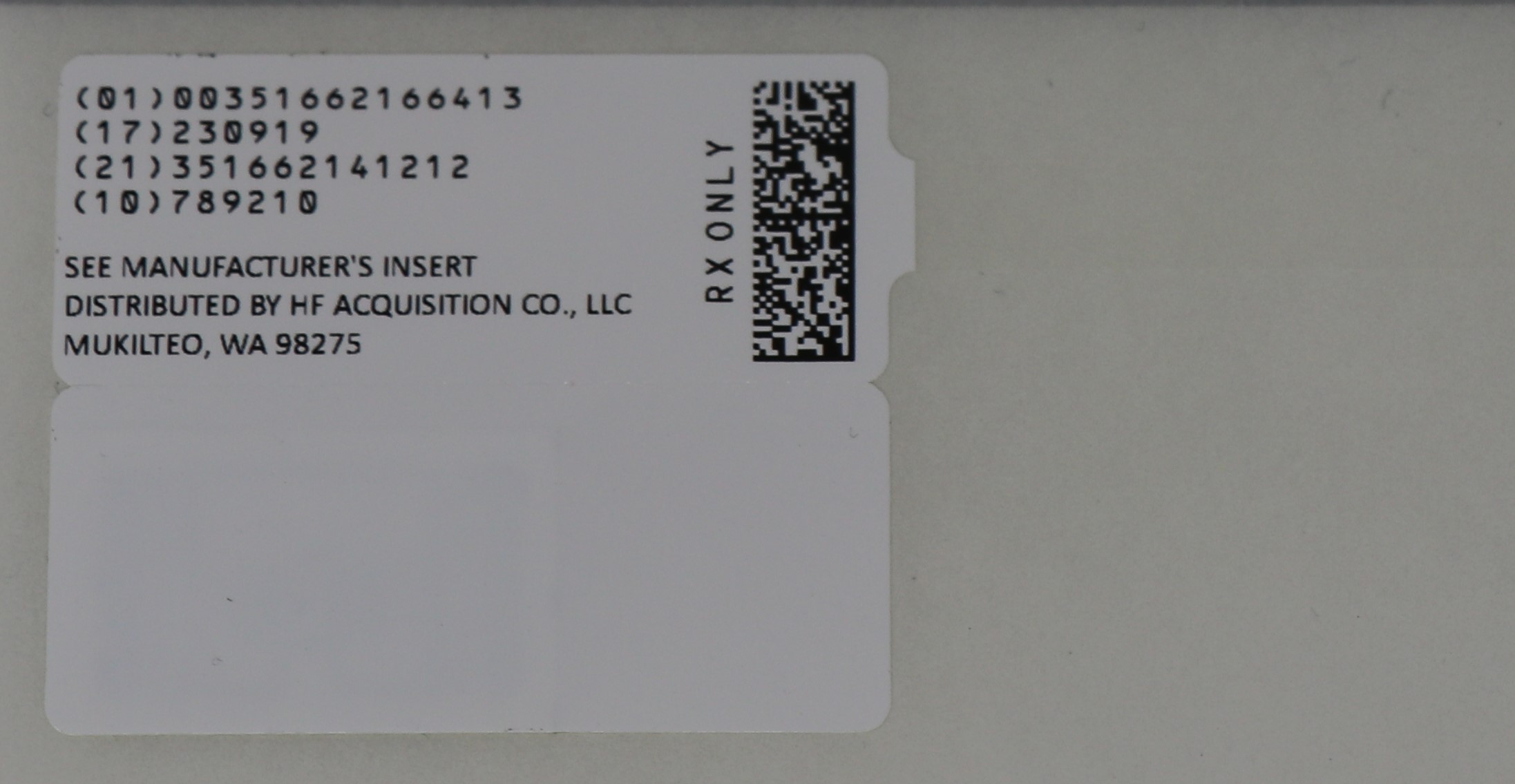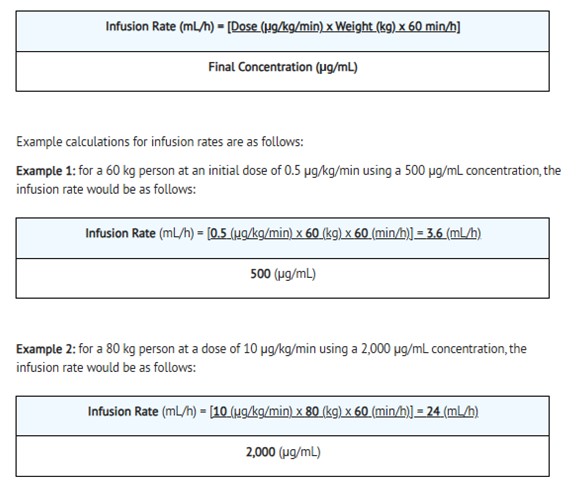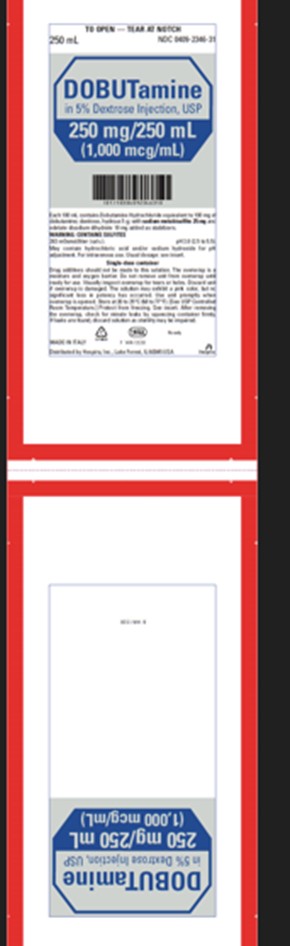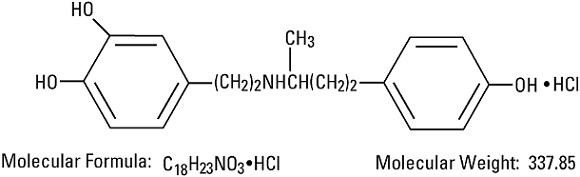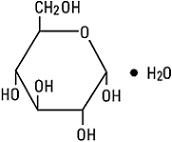 DRUG LABEL: DOBUTAMINE IN DEXTROSE
NDC: 51662-1664 | Form: INJECTION, SOLUTION
Manufacturer: HF Acquisition Co. LLC, DBA HealthFirst
Category: prescription | Type: HUMAN PRESCRIPTION DRUG LABEL
Date: 20260106

ACTIVE INGREDIENTS: DOBUTAMINE HYDROCHLORIDE 100 mg/100 mL
INACTIVE INGREDIENTS: DEXTROSE MONOHYDRATE 5 g/100 mL; SODIUM METABISULFITE 25 mg/100 mL; SODIUM HYDROXIDE; WATER; HYDROCHLORIC ACID; EDETATE DISODIUM 10 mg/100 mL

DOBUTamine
in 5% Dextrose Injection, USP
Flexible Plastic Container

DESCRIPTION

Dobutamine in 5% Dextrose Injection, USP is a sterile, nonpyrogenic, prediluted solution of dobutamine hydrochloride and dextrose in water for injection. It is administered by intravenous infusion.

Each 100 mL contains dobutamine hydrochloride equivalent to 100 mg, 200 mg, or 400 mg of dobutamine; dextrose (derived from corn), hydrous 5 g in water for injection, with sodium metabisulfite 25 mg and edetate disodium, dihydrate 10 mg added as stabilizers; osmolar concentration, respectively, 263, 270, or 284 mOsmol/liter (calc.). The pH is 3.0 (2.5 to 5.5). May contain hydrochloric acid and/or sodium hydroxide for pH adjustment. Dobutamine in 5% Dextrose Injection, USP is oxygen sensitive.

Dobutamine Hydrochloride, USP is chemically designated (±)-4-[2-[[3-(p-hydroxyphenyl)-1-methylpropyl]amino]ethyl]-pyrocatechol hydrochloride. It is a synthetic catecholamine.

Dextrose, USP is chemically designated D-glucose monohydrate (C6H12O6 • H2O), a hexose sugar freely soluble in water. It has the following structural formula:

Water for Injection, USP is chemically designated H2O.

The flexible plastic container is fabricated from a specially formulated CR3 plastic material. Water can permeate from inside the container into the overwrap but not in amounts sufficient to affect the solution significantly. Solutions in contact with the plastic container may leach out certain chemical components from the plastic in very small amounts; however, biological testing was supportive of the safety of the plastic container materials. Exposure to temperatures above 25°C/77°F during transport and storage will lead to minor losses in moisture content. Higher temperatures lead to greater losses. It is unlikely that these minor losses will lead to clinically significant changes within the expiration period.

CLINICAL PHARMACOLOGY

Dobutamine is a direct-acting inotropic agent whose primary activity results from stimulation of the β-receptors of the heart while producing comparatively mild chronotropic, hypertensive, arrhythmogenic, and vasodilative effects. It does not cause the release of endogenous norepinephrine, as does dopamine. In animal studies, dobutamine produces less increase in heart rate and less decrease in peripheral vascular resistance for a given inotropic effect than does isoproterenol.

In patients with depressed cardiac function, both dobutamine and isoproterenol increase the cardiac output to a similar degree. In the case of dobutamine, this increase is usually not accompanied by marked increases in heart rate (although tachycardia is occasionally observed), and the cardiac stroke volume is usually increased. In contrast, isoproterenol increases the cardiac index primarily by increasing the heart rate while stroke volume changes little or declines.

Facilitation of atrioventricular conduction has been observed in human electrophysiologic studies and in patients with atrial fibrillation.

Systemic vascular resistance is usually decreased with administration of dobutamine. Occasionally, minimum vasoconstriction has been observed.

Most clinical experience with dobutamine is short-term, not more than several hours in duration. In the limited number of patients who were studied for 24, 48, and 72 hours, a persistent increase in cardiac output occurred in some, whereas output returned toward baseline values in others.

The onset of action of Dobutamine in 5% Dextrose Injection, USP is within 1 to 2 minutes; however, as much as 10 minutes may be required to obtain the peak effect of a particular infusion rate.

The plasma half-life of dobutamine in humans is 2 minutes. The principal routes of metabolism are methylation of the catechol and conjugation. In human urine, the major excretion products are the conjugates of dobutamine and 3-O-methyl dobutamine. The 3-O-methyl derivative of dobutamine is inactive.

Alteration of synaptic concentrations of catecholamines with either reserpine or tricyclic antidepressants does not alter the actions of dobutamine in animals, which indicates that the actions of dobutamine are not dependent on presynaptic mechanisms.

The effective infusion rate of dobutamine varies widely from patient to patient, and titration is always necessary (see DOSAGE AND ADMINISTRATION). At least in pediatric patients, dobutamine-induced increases in cardiac output and systemic pressure are generally seen, in any given patient, at lower infusion rates than those that cause substantial tachycardia (see PRECAUTIONS, Pediatric Use).

INDICATIONS AND USAGE

Dobutamine in 5% Dextrose Injection, USP is indicated when parenteral therapy is necessary for inotropic support in the short-term treatment of patients with cardiac decompensation due to depressed contractility resulting either from organic heart disease or from cardiac surgical procedures. Experience with intravenous dobutamine in controlled trials does not extend beyond 48 hours of repeated boluses and/or continuous infusions.

Whether given orally, continuously intravenously, or intermittently intravenously, neither dobutamine nor any other cyclic-AMP-dependent inotrope has been shown in controlled trials to be safe or effective in the long-term treatment of congestive heart failure. In controlled trials of chronic oral therapy with various such agents, symptoms were not consistently alleviated, and the cyclic-AMP-dependent inotropes were consistently associated with increased risks of hospitalization and death. Patients with NYHA Class IV symptoms appeared to be at particular risk.

CONTRAINDICATIONS

Dobutamine in 5% Dextrose Injection, USP is contraindicated in patients with idiopathic hypertrophic subaortic stenosis and in patients who have shown previous manifestations of hypersensitivity to dobutamine or any of its components.

WARNINGS

Increase in Heart Rate or Blood Pressure

Dobutamine hydrochloride may cause a marked increase in heart rate or blood pressure, especially systolic pressure. Approximately 10% of adult patients in clinical studies have had rate increases of 30 beats/minute or more, and about 7.5% have had a 50-mm Hg or greater increase in systolic pressure. Usually, reduction of dosage reverses these effects.

Because dobutamine facilitates atrioventricular conduction, patients with atrial fibrillation are at risk of developing rapid ventricular response. In patients who have atrial fibrillation with rapid ventricular response, a digitalis preparation should be used prior to institution of therapy with dobutamine. Patients with pre-existing hypertension appear to face an increased risk of developing an exaggerated pressure response.

Ectopic Activity

Dobutamine may precipitate or exacerbate ventricular ectopic activity, but it rarely has caused ventricular tachycardia.

Hypersensitivity

Reactions suggestive of hypersensitivity associated with administration of Dobutamine in 5% Dextrose Injection, USP, including skin rash, fever, eosinophilia, and bronchospasm, have been reported occasionally.

Dobutamine in 5% Dextrose Injection, USP contains sodium bisulfite, a sulfite that may cause allergic-type reactions, including anaphylactic symptoms and life-threatening or less severe asthmatic episodes, in certain susceptible people. The overall prevalence of sulfite sensitivity in the general population is unknown and probably low. Sulfite sensitivity is seen more frequently in asthmatic than in nonasthmatic people.

PRECAUTIONS

General

During the administration of dobutamine, as with any adrenergic agent, ECG and blood pressure should be continuously monitored. In addition, pulmonary wedge pressure and cardiac output should be monitored whenever possible to aid in the safe and effective infusion of Dobutamine in 5% Dextrose Injection, USP.

Hypovolemia should be corrected with suitable volume expanders before treatment with Dobutamine in 5% Dextrose Injection, USP is instituted.

Animal studies indicate that dobutamine may be ineffective if the patient has recently received a β-blocking drug. In such a case, the peripheral vascular resistance may increase.

No improvement may be observed in the presence of marked mechanical obstruction, such as severe valvular aortic stenosis.

Do not administer unless solution is clear and container is undamaged. Discard unused portion.

Usage Following Acute Myocardial Infarction: Clinical experience with dobutamine following myocardial infarction has been insufficient to establish the safety of the drug for this use. There is concern that any agent that increases contractile force and heart rate may increase the size of an infarction by intensifying ischemia, but it is not known whether dobutamine does so.

Drug Interactions: There was no evidence of drug interactions in clinical studies in which dobutamine hydrochloride was administered concurrently with other drugs, including digitalis preparations, furosemide, spironolactone, lidocaine, glyceryl trinitrate, isosorbide dinitrate, morphine, atropine, heparin, protamine, potassium chloride, folic acid, and acetaminophen. Preliminary studies indicate that the concomitant use of dobutamine and nitroprusside results in a higher cardiac output and, usually, a lower pulmonary wedge pressure than when either drug is used alone.

Concomitant use of dobutamine and catechol-O-methyltranferase (COMT) inhibitors (e.g., entacapone) may result in increased heart rate, arrhythmias, and changes in blood pressure.

Carcinogenesis, Mutagenesis, Impairment of Fertility: Studies to evaluate the carcinogenic or mutagenic potential of dobutamine or the potential of the drug to affect fertility adversely have not been performed.

Pregnancy: Reproduction studies performed in rats and rabbits have revealed no evidence of harm to the fetus due to dobutamine. The drug, however, has not been administered to pregnant women and should be used only when the expected benefits clearly outweigh the potential risks to the fetus.

Pediatric Use: Dobutamine has been shown to increase cardiac output and systemic pressure in pediatric patients of every age group. In premature neonates, however, dobutamine is less effective than dopamine in raising systemic blood pressure without causing undue tachycardia, and dobutamine has not been shown to provide any added benefit when given to such infants already receiving optimal infusions of dopamine.

Geriatric Use: Clinical studies of dobutamine did not include sufficient numbers of subjects aged 65 and over to determine whether they respond differently from younger subjects. Other reported clinical experience has not identified differences in responses between the elderly and younger patients. In general, dose selection for an elderly patient should be cautious, usually starting at the low end of the dosing range, reflecting the greater frequency of decreased hepatic, renal, or cardiac function, and of concomitant disease or drug therapy.

ADVERSE REACTIONS

Increased Heart Rate, Blood Pressure, and Ventricular Ectopic Activity: A 10- to 20-mm Hg increase in systolic blood pressure and an increase in heart rate of 5 to 15 beats/minute have been noted in most patients (see WARNINGS regarding exaggerated chronotropic and pressor effects). Approximately 5% of adult patients have had increased premature ventricular beats during infusions. These effects are dose related.

Hypotension: Precipitous decreases in blood pressure have occasionally been described in association with dobutamine therapy. Decreasing the dose or discontinuing the infusion typically results in rapid return of blood pressure to baseline values. In rare cases, however, intervention may be required and reversibility may not be immediate.

Stress Cardiomyopathy: Stress cardiomyopathy has been reported with dobutamine in association with cardiac stress testing.

Reactions at Sites of Intravenous Infusion: Phlebitis has occasionally been reported. Local inflammatory changes have been described following inadvertent infiltration.

Miscellaneous Uncommon Effects: The following adverse effects have been reported in 1% to 3% of adult patients: nausea, headache, anginal pain, nonspecific chest pain, palpitations, and shortness of breath.

Administration of dobutamine, like other catecholamines, has been associated with decreases in serum potassium concentrations, rarely to hypokalemic values.

OVERDOSAGE

Overdoses of dobutamine have been reported rarely. The following is provided to serve as a guide if such an overdose is encountered.

Signs and Symptoms: Toxicity from dobutamine hydrochloride is usually due to excessive cardiac β-receptor stimulation. The duration of action of dobutamine hydrochloride is generally short (T½ = 2 minutes) because it is rapidly metabolized by catechol-O-methyltransferase. The symptoms of toxicity may include anorexia, nausea, vomiting, tremor, anxiety, palpitations, headache, shortness of breath, and anginal and nonspecific chest pain. The positive inotropic and chronotropic effects of dobutamine on the myocardium may cause hypertension, tachyarrhythmias, myocardial ischemia, and ventricular fibrillation. Hypotension may result from vasodilation.

If the product is ingested, unpredictable absorption may occur from the mouth and the gastrointestinal tract.

Treatment: To obtain up-to-date information about the treatment of overdose, a good resource is your certified Regional Poison Control Center. Telephone numbers of certified poison control centers are listed in the Physicians' Desk Reference (PDR). In managing overdosage, consider the possibility of multiple drug overdoses, interaction among drugs, and unusual drug kinetics in your patient.

The initial actions to be taken in a dobutamine hydrochloride overdose are discontinuing administration, establishing an airway, and ensuring oxygenation and ventilation. Resuscitative measures should be initiated promptly. Severe ventricular tachyarrhythmias may be successfully treated with propranolol or lidocaine. Hypertension usually responds to a reduction in dose or discontinuation of therapy.

Protect the patient's airway and support ventilation and perfusion. If needed, meticulously monitor and maintain, within acceptable limits, the patient's vital signs, blood gases, serum electrolytes, etc. Absorption of drugs from the gastrointestinal tract may be decreased by giving activated charcoal, which, in many cases, is more effective than emesis or lavage; consider charcoal instead of or in addition to gastric emptying. Repeated doses of charcoal over time may hasten elimination of some drugs that have been absorbed. Safeguard the patient's airway when employing gastric emptying or charcoal.

Forced diuresis, peritoneal dialysis, hemodialysis, or charcoal hemoperfusion have not been established as beneficial for an overdose of dobutamine hydrochloride.

Recommended Dosage

Dobutamine in 5% Dextrose Injection, USP is administered intravenously through a suitable intravenous catheter or needle. A calibrated electronic infusion device is recommended for controlling the rate of flow in mL/hour or drops/minute. Infusion of dobutamine should be started at a low rate (0.5 to 1.0 µg/kg/min) and titrated at intervals of a few minutes, guided by the patient's response, including systemic blood pressure, urine flow, frequency of ectopic activity, heart rate, and (whenever possible) measurements of cardiac output, central venous pressure, and/or pulmonary capillary wedge pressure. In reported trials, the optimal infusion rates have varied from patient to patient, usually 2 to 20 µg/kg/min but sometimes slightly outside of this range. On rare occasions, infusion rates up to 40 µg/kg/min have been required to obtain the desired effect.

Rates of infusion in mL/hour for dobutamine hydrochloride concentrations of 500, 1,000, 2,000 and 4,000 mg/L may be calculated using the following formula:

This container system may be inappropriate for the dosage requirements of pediatric patients under 30 kg.

Parenteral drug products should be inspected visually for particulate matter and discoloration prior to administration whenever solution and container permit.

Dobutamine in 5% Dextrose Injection, USP solutions may exhibit a pink color that, if present, will increase with time. This color change is due to slight oxidation of the drug, but there is no significant loss of potency.

Solutions containing dextrose should not be administered through the same administration set as blood, as this may result in pseudoagglutination or hemolysis.

Do not add supplementary medications to Dobutamine in 5% Dextrose Injection, USP. Do not administer Dobutamine in 5% Dextrose Injection, USP simultaneously with solutions containing sodium bicarbonate or strong alkaline solutions.

INSTRUCTIONS FOR USE

To Open

Tear outer wrap at notch and remove solution container. Some opacity of the plastic due to moisture absorption during the sterilization process may be observed. This is normal and does not affect the solution quality or safety. The opacity will diminish gradually.

Preparation for Administration

(Use aseptic technique)

1.
Close flow control clamp of administration set.
2.
Remove cover from outlet port at bottom of container.
3.
Insert piercing pin of administration set into port with a twisting motion until the set is firmly seated.
NOTE: See full directions on administration set carton.
4.
Suspend container from hanger.
5.
Squeeze and release drip chamber to establish proper fluid level in chamber.
6.
Open flow control clamp and clear air from set. Close clamp.
7.
Attach set to venipuncture device. If device is not indwelling, prime and make venipuncture.
8.
Regulate rate of administration with flow control clamp.

WARNING: Do not use flexible container in series connections.

HOW SUPPLIED

DOBUTamine in 5% Dextrose Injection, USP is supplied in 250 LifeCare™ single-dose flexible containers as follows:

NDC 51662-1664-2 250 mg/250 mL
(1 mg/mL)

Do not freeze. Store at 20°C to 25°C (68°F to 77°F). [See USP Controlled Room Temperature.]

Distributed by HF Acquisition Co LLC dba HealthFirst